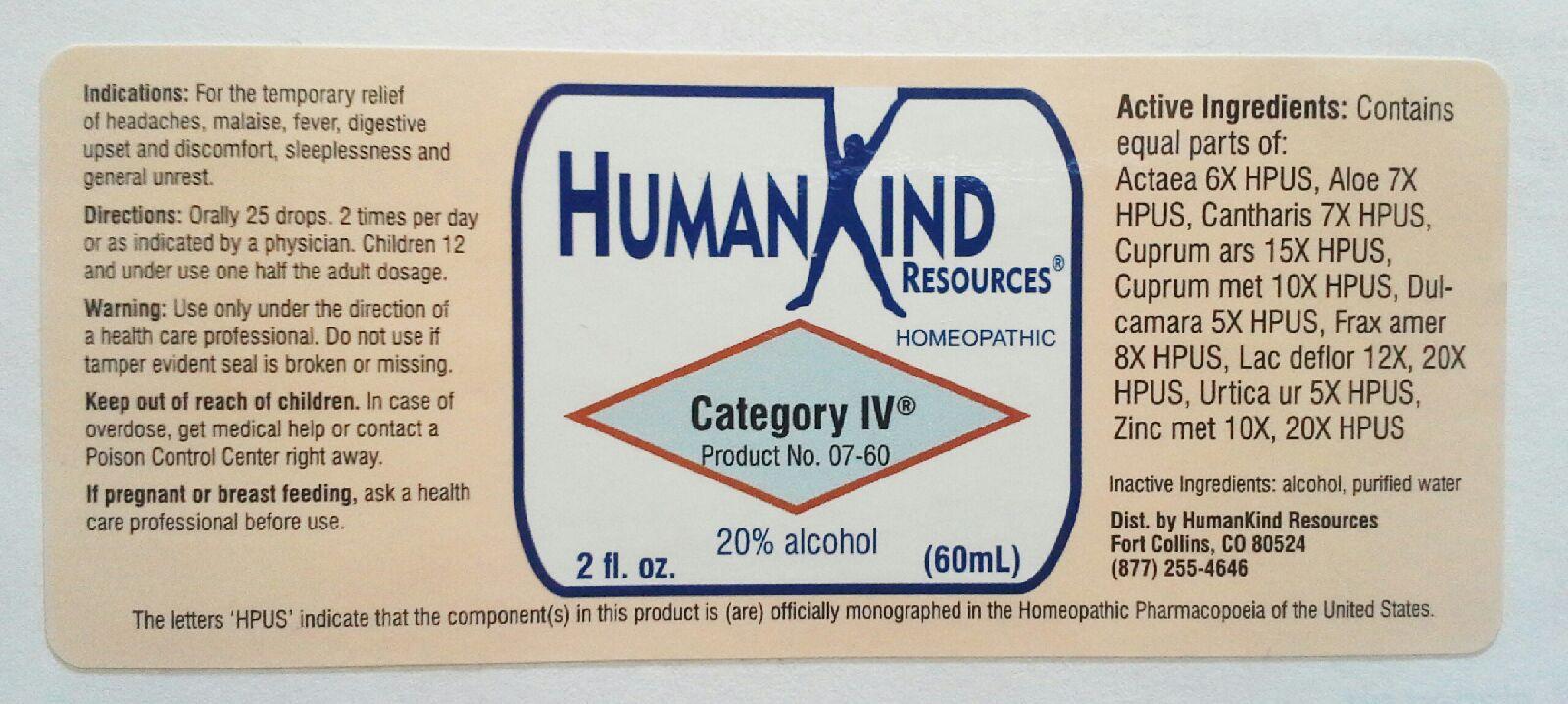 DRUG LABEL: Category IV
NDC: 64616-085 | Form: LIQUID
Manufacturer: Vitality Works, Inc.
Category: homeopathic | Type: HUMAN OTC DRUG LABEL
Date: 20251217

ACTIVE INGREDIENTS: ACTAEA SPICATA ROOT 6 [hp_X]/1 mL; ALOE 7 [hp_X]/1 mL; LYTTA VESICATORIA 7 [hp_X]/1 mL; CUPRIC ARSENITE 15 [hp_X]/1 mL; COPPER 10 [hp_X]/1 mL; SOLANUM DULCAMARA TOP 5 [hp_X]/1 mL; SKIM MILK 20 [hp_X]/1 mL; FRAXINUS AMERICANA BARK 8 [hp_X]/1 mL; URTICA URENS 5 [hp_X]/1 mL; ZINC 20 [hp_X]/1 mL
INACTIVE INGREDIENTS: ALCOHOL; WATER

Category IV

Category IV

Actaea Spicata 6X Dulcamara 5X

Aloe Socotrina 7X Fraxinus Americana 8X

Cantharis 7X La Defloratum 12X, 20X

Cuprum Arsenicosum 15X Urtica Urens 5X

Cuprum Metallicum 10X Zinc Metallicum 10X, 20X

Category IV

Alcohol, Purified Water

Category IV

Use only under the direction of a health care professional. Do not use if tamper evident seal is broken or missing.

Category IV

Keep out of reach of children. In case of overdose, get medical help or contact a Poison Control Center right away.

Category IV

For the temporary relief of headaches, malaise, fever, digestive upset and discomfort, sleeplessness and general unrest.

Category IV

Orally 25 drops, 2 times per day or as indicated by a physician. Children 12 and under use one half the adult dosage.

Category IV

Temporarly relieves headaches, malaise, fever, digestive upset and discomfort, sleeplessness and general unrest.